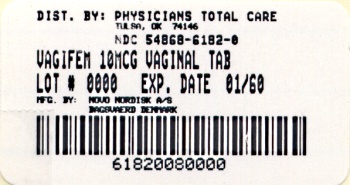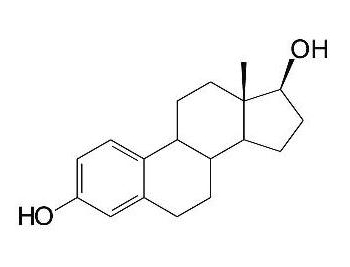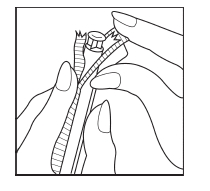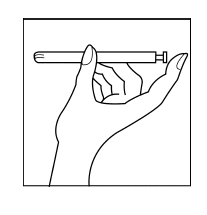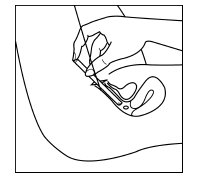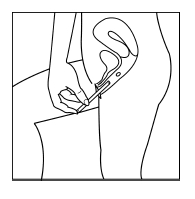 DRUG LABEL: Vagifem
NDC: 54868-6182 | Form: TABLET, FILM COATED
Manufacturer: Physicians Total Care, Inc.
Category: prescription | Type: HUMAN PRESCRIPTION DRUG LABEL
Date: 20120315

ACTIVE INGREDIENTS: ESTRADIOL 10 ug/1 1
INACTIVE INGREDIENTS: HYPROMELLOSES 54.212 mg/1 1

HIGHLIGHTS OF PRESCRIBING INFORMATION

These highlights do not include all the information needed to use Vagifem safely and effectively. See full prescribing information for Vagifem.
Vagifem® (estradiol vaginal tablets)
Initial U.S. Approval: 1999

WARNING: CARDIOVASCULAR DISORDERS, ENDOMETRIAL CANCER, BREAST CANCER and PROBABLE DEMENTIA

See full prescribing information for complete boxed warning

Estrogen-Alone Therapy

- There is an increased risk of endometrial cancer in a woman with a uterus who uses unopposed estrogens (5.3)
- Estrogen-alone therapy should not be used for the prevention of cardiovascular disease or dementia (5.2, 5.4)
- The Women’s Health Initiative (WHI) estrogen-alone substudy reported increased risks of stroke and deep vein thrombosis (DVT) (5.2)
- The WHI Memory Study (WHIMS) estrogen-alone ancillary study of WHI reported an increased risk of probable dementia in postmenopausal women 65 years of age and older (5.4)

Estrogen Plus Progestin Therapy

- Estrogen plus progestin therapy should not be used for the prevention of cardiovascular disease or dementia (5.2, 5.4)
- The WHI estrogen plus progestin substudy reported increased risks of stroke, DVT, pulmonary embolism, and myocardial infarction (5.2)
- The WHI estrogen plus progestin substudy reported increased risks of invasive breast cancer (5.3)
- The WHIMS estrogen plus progestin ancillary study of WHI reported an increased risk of probable dementia in postmenopausal women 65 years of age and older (5.4)

1 INDICATIONS AND USAGE

Vagifem is an estrogen (estradiol) indicated for the treatment of atrophic vaginitis due to menopause (1).

2 DOSAGE AND ADMINISTRATION

Vagifem should be administered intravaginally:

- 1 tablet daily for 2 weeks, followed by 1 tablet twice weekly (for example, Tuesday and Friday) (2.2)

3 DOSAGE FORMS AND STRENGTHS

- Vagifem 10 mcg tablet: One vaginal tablet contains 10.3 mcg of estradiol hemihydrate equivalent to 10 mcg of estradiol (3)
- Vagifem 25 mcg tablet: One vaginal tablet contains 25.8 mcg of estradiol hemihydrate equivalent to 25 mcg of estradiol (3)

4 CONTRAINDICATIONS

- Undiagnosed abnormal genital bleeding (4)
- Known, suspected, or history of breast cancer (4, 5.3)
- Known or suspected estrogen-dependent neoplasia (4, 5.3)
- Active deep vein thrombosis, pulmonary embolism or history of these conditions (4, 5.2)
- Active arterial thromboembolic disease (for example, stroke and myocardial infarction), or a history of these conditions (4, 5.2)
- Known liver dysfunction or disease (4, 5.11)
- Known or suspected pregnancy (4, 8.1)

5 WARNINGS AND PRECAUTIONS

- Estrogens increase the risk of gallbladder disease (5.5)
- Discontinue estrogen if severe hypercalcemia, loss of vision, severe hypertriglyceridemia or cholestatic jaundice occurs (5.6 , 5.7 , 5.10, 5.11)
- The Vagifem applicator may cause vaginal abrasion (5.17)
- Monitor thyroid function in women on thyroid replacement therapy (5.12 , 5.19)

6 ADVERSE REACTIONS

In prospective, randomized, placebo-controlled, double-blind studies the most common adverse reactions (incidence ≥5 percent) were upper respiratory tract infection, headache, abdominal pain, back pain, genital pruritis, moniliasis, vulvovaginal mycotic infection and diarrhea (6.1).

To report SUSPECTED ADVERSE REACTIONS, contact Novo Nordisk at 1-888-824-4336 or FDA at 1-800-FDA-1088 or www.fda.gov/medwatch.

7 DRUG INTERACTIONS

- Inducers and inhibitors of CYP3A4 may affect estrogen drug metabolism (7.1)

8 USE IN SPECIFIC POPULATIONS

- Nursing Women: Estrogen administration to nursing women has been shown to decrease the quantity and quality of breast milk (8.3)
- Geriatric Use: An increased risk of probable dementia in women over 65 years of age was reported in the Women’s Health Initiative Memory ancillary studies of the Women’s Health Initiative (8.5)

FULL PRESCRIBING INFORMATION

WARNING: CARDIOVASCULAR DISORDERS, ENDOMETRIAL CANCER, BREAST CANCER and PROBABLE DEMENTIA

Estrogen-Alone Therapy

Endometrial Cancer

There is an increased risk of endometrial cancer in a woman with a uterus who uses unopposed estrogens. Adding a progestin to estrogen therapy has been shown to reduce the risk of endometrial hyperplasia, which may be a precursor to endometrial cancer. Adequate diagnostic measures, including directed or random endometrial sampling when indicated, should be undertaken to rule out malignancy in postmenopausal women with undiagnosed persistent or recurring abnormal genital bleeding [see Warnings and Precautions (5.3)].

Cardiovascular Disorders and Probable Dementia

Estrogen-alone therapy should not be used for the prevention of cardiovascular disease or dementia [see Warnings and Precautions (5.2),(5.4), and Clinical Studies (14.2),(14.3)].

The Women's Health Initiative (WHI) estrogen-alone substudy reported increased risks of stroke and deep vein thrombosis (DVT) in postmenopausal women (50 to 79 years of age) during 7.1 years of treatment with daily oral conjugated estrogens (CE) [0.625 mg], relative to placebo [see Warnings and Precautions (5.2), and Clinical Studies (14.2)].

The WHI Memory Study (WHIMS) estrogen-alone ancillary study of WHI reported an increased risk of developing probable dementia in postmenopausal women 65 years of age or older during 5.2 years of treatment with daily CE (0.625 mg) alone, relative to placebo. It is unknown whether this finding applies to younger postmenopausal women [see Warnings and Precautions (5.4) , Use in Specific Populations (8.5), and Clinical Studies (14.3)].

In the absence of comparable data, these risks should be assumed to be similar for other doses of CE and other dosage forms of estrogens.

Estrogens with or without progestins should be prescribed at the lowest effective doses and for the shortest duration consistent with treatment goals and risks for the individual woman.

Estrogen Plus Progestin Therapy

Cardiovascular Disorders and Probable Dementia

Estrogen plus progestin therapy should not be used for the prevention of cardiovascular disease or dementia [see Warnings and Precautions (5.2),(5.4) and Clinical Studies (14.2),(14.3)].

The WHI estrogen plus progestin substudy reported increased risks of DVT, pulmonary embolism, stroke and myocardial infarction in postmenopausal women (50 to 79 years of age) during 5.6 years of treatment with daily oral CE (0.625 mg) combined with medroxyprogesterone acetate (MPA) [2.5 mg], relative to placebo [see Warnings and Precautions (5.2), and Clinical Studies (14.2)].

The WHIMS estrogen plus progestin ancillary study of the WHI, reported an increased risk of developing probable dementia in postmenopausal women 65 years of age or older during 4 years of treatment with daily CE (0.625 mg) combined with MPA (2.5 mg), relative to placebo. It is unknown whether this finding applies to younger postmenopausal women [ see Warnings and Precautions (5.4), Use in Specific Populations (8.5), and Clinical Studies (14.3)].

Breast Cancer

The WHI estrogen plus progestin substudy also demonstrated an increased risk of invasive breast cancer [see Warnings and Precautions (5.3), and Clinical Studies (14.2)].

In the absence of comparable data, these risks should be assumed to be similar for other doses of CE and MPA, and other combinations and dosage forms of estrogens and progestins.

Estrogens with or without progestins should be prescribed at the lowest effective doses and for the shortest duration consistent with treatment goals and risks for the individual woman.

2 DOSAGE AND ADMINISTRATION

2.1 General Dosing Information

Generally, when estrogen is prescribed for a postmenopausal woman with a uterus, a progestin should also be considered to reduce the risk of endometrial cancer.

A woman without a uterus does not need a progestin. In some cases, however, hysterectomized women with a history of endometriosis may need a progestin [see Warnings and Precautions (5.3), 5.15)].

Use of estrogen-alone, or in combination with a progestin, should be with the lowest effective dose and for the shortest duration consistent with treatment goals and risks for the individual woman. Postmenopausal women should be re-evaluated periodically as clinically appropriate to determine if treatment is still necessary.

2.2 Recommended Dosing

Vagifem should be administered intravaginally using the supplied applicator: 1 tablet daily for 2 weeks, followed by 1 tablet twice weekly (for example, Tuesday and Friday). Generally, women should be started at the 10 mcg dosage strength.

3 DOSAGE FORMS AND STRENGTHS

Vagifem is a small, white, round, film-coated, bi-convex vaginal tablet containing 10 mcg or 25 mcg of estradiol. Each vaginal tablet is 6 mm in diameter and is administered in a disposable applicator.

4 CONTRAINDICATIONS

Vagifem should not be used in women with any of the following conditions:

- Undiagnosed abnormal genital bleeding
- Known, suspected, or history of breast cancer
- Known or suspected estrogen-dependent neoplasia
- Active deep vein thrombosis, pulmonary embolism or history of these conditions
- Active arterial thromboembolic disease (for example, stroke, and myocardial infarction), or a history of these conditions
- Known liver dysfunction or disease
- Known or suspected pregnancy

5 WARNINGS AND PRECAUTIONS

5.1 Risks From Systemic Absorption

Vagifem is intended only for vaginal administration. Systemic absorption occurs with the use of Vagifem. The warnings, precautions, and adverse reactions associated with the use of systemic estrogen therapy should be taken into account.

5.2 Cardiovascular Disorders

An increased risk of stroke and deep vein thrombosis (DVT) has been reported with estrogen-alone therapy. An increased risk of pulmonary embolism, DVT, stroke, and myocardial infarction has been reported with estrogen plus progestin therapy. Should any of these occur or be suspected, estrogens with or without progestins should be discontinued immediately.

Risk factors for arterial vascular disease (for example, hypertension, diabetes mellitus, tobacco use, hypercholesterolemia, and obesity) and/or venous thromboembolism (for example, personal history or family history of venous thromboembolism [VTE], obesity, and systemic lupus erythematosus) should be managed appropriately.

Stroke

In the Women’s Health Initiative (WHI) estrogen-alone substudy, a statistically significant increased risk of stroke was reported in women 50 to 79 years of age receiving daily CE (0.625 mg) compared to women in the same age group receiving placebo (45 versus 33 per 10,000 women-years). The increase in risk was demonstrated in year one and persisted [see Clinical Studies (14.2)]. Should a stroke occur or be suspected, estrogens should be discontinued immediately.

Subgroup analyses of women 50 to 59 years of age suggest no increased risk of stroke for those women receiving CE (0.625 mg) versus those receiving placebo (18 versus 21 per 10,000 women-years).^1

In the WHI estrogen plus progestin substudy, a statistically significant increased risk of stroke was reported in all women receiving daily CE (0.625 mg) plus MPA (2.5 mg) compared to placebo (33 versus 25 per 10,000 women-years) [see Clinical Studies (14.2)]. The increase in risk was demonstrated after the first year and persisted.^1

Coronary Heart Disease

In the WHI estrogen - alone substudy, no overall effect on coronary heart disease (CHD) events (defined as non-fatal myocardial infarction [MI], silent MI, or CHD death) was reported in women receiving estrogen alone compared to placebo^2 [see Clinical Studies (14.2)].

Subgroup analysis of women 50 to 59 years of age suggests a statistically non-significant reduction in CHD events (CE 0.625 mg compared to placebo) in women with less than 10 years since menopause (8 versus 16 per 10,000 women-years).^1

In the WHI estrogen plus progestin substudy, there was a statistically non-significant increased risk of CHD events in women receiving daily CE (0.625 mg) plus MPA (2.5 mg) compared to women receiving placebo (41 versus 34 per 10,000 women-years).^1 An increase in relative risk was demonstrated in year 1, and a trend toward decreasing relative risk was reported in years 2 through 5 [see Clinical Studies (14.2)].

In postmenopausal women with documented heart disease (n=2,763), average age 66.7 years, in a controlled clinical trial of secondary prevention of cardiovascular disease (Heart and Estrogen/Progestin Replacement Study [HERS]) treatment with daily CE (0.625 mg) plus MPA (2.5 mg) demonstrated no cardiovascular benefit. During an average follow-up of 4.1 years, treatment with CE plus MPA did not reduce the overall rate of CHD events in postmenopausal women with established coronary heart disease. There were more CHD events in the CE plus MPA-treated group than in the placebo group in year 1, but not during the subsequent years. Two thousand, three hundred and twenty-one (2,321) women from the original HERS trial agreed to participate in an open label extension of the original HERS, HERS II. Average follow-up in HERS II was an additional 2.7 years, for a total of 6.8 years overall. Rates of CHD events were comparable among women in the CE (0.625 mg) plus MPA (2.5 mg) group and the placebo group in HERS, HERS II, and overall.

Venous Thromboembolism (VTE)

In the WHI estrogen-alone substudy, the risk of VTE (DVT and pulmonary embolism [PE]) was increased for women receiving daily CE (0.625 mg) compared to placebo (30 versus 22 per 10,000 women-years), although only the increased risk of DVT reached statistical significance (23 versus 15 per 10,000 women-years). The increase in VTE risk was demonstrated during the first 2 years^3 [see Clinical Studies (14.2)]. Should a VTE occur or be suspected, estrogens should be discontinued immediately.

In the WHI estrogen plus progestin substudy, a statistically significant 2-fold greater rate of VTE was reported in women receiving daily CE (0.625 mg) plus MPA (2.5 mg) compared to women receiving placebo (35 versus 17 per 10,000 women-years). Statistically significant increases in risk for both DVT (26 versus 13 per 10,000 women-years) and PE (18 versus 8 per 10,000 women-years) were also demonstrated. The increase in VTE risk was observed during the first year and persisted^4 [see Clinical Studies (14.2)]. Should a VTE occur or be suspected, estrogens should be discontinued immediately.

If feasible, estrogens should be discontinued at least 4 to 6 weeks before surgery of the type associated with an increased risk of thromboembolism, or during periods of prolonged immobilization.

5.3 Malignant Neoplasms

Endometrial Cancer

An increased risk of endometrial cancer has been reported with the use of unopposed estrogen therapy in women with a uterus. The reported endometrial cancer risk among unopposed estrogen users is about 2- to 12-fold greater than in non-users, and appears dependent on duration of treatment and on estrogen dose. Most studies show no significant increased risk associated with use of estrogens for less than 1 year. The greatest risk appears associated with prolonged use, with an increased risk of 15- to 24-fold for 5 to 10 years or more and this risk has been shown to persist for at least 8 to 15 years after estrogen therapy is discontinued.

Clinical surveillance of all women using estrogen-alone or estrogen plus progestin therapy is important. Adequate diagnostic measures, including directed or random endometrial sampling when indicated, should be undertaken to rule out malignancy in postmenopausal women with undiagnosed persistent or recurring abnormal genital bleeding.

There is no evidence that the use of natural estrogens results in a different endometrial risk profile than synthetic estrogens of equivalent estrogen dose. Adding a progestin to estrogen therapy in postmenopausal women has been shown to reduce the risk of endometrial hyperplasia, which may be a precursor to endometrial cancer.

Breast Cancer

The most important randomized clinical trial providing information about breast cancer in estrogen-alone users is the Women’s Health Initiative (WHI) substudy of daily CE (0.625 mg). In the WHI estrogen-alone substudy, after an average follow-up of 7.1 years, daily CE (0.625 mg) was not associated with an increased risk of invasive breast cancer [relative risk (RR) 0.80] ^5 [see Clinical Studies (14.2)].

The most important randomized clinical trial providing information about breast cancer in estrogen plus progestin users is the WHI substudy of daily CE (0.625 mg) plus MPA (2.5 mg). After a mean follow-up of 5.6 years, the estrogen plus progestin substudy reported an increased risk of breast cancer in women who took daily CE plus MPA. In this substudy, prior use of estrogen-alone or estrogen plus progestin therapy was reported by 26 percent of the women. The relative risk of invasive breast cancer was 1.24, and the absolute risk was 41 versus 33 cases per 10,000 women-years, for estrogen plus progestin compared with placebo.^6 Among women who reported prior use of hormone therapy, the relative risk of invasive breast cancer was 1.86, and the absolute risk was 46 versus 25 cases per 10,000 women-years for estrogen plus progestin compared with placebo. Among women who reported no prior use of hormone therapy, the relative risk of invasive breast cancer was 1.09, and the absolute risk was 40 versus 36 cases per 10,000 women-years for estrogen plus progestin compared with placebo. In the same substudy, invasive breast cancers were larger and diagnosed at a more advanced stage in the CE (0.625 mg) plus MPA (2.5 mg) group compared with the placebo group. Metastatic disease was rare, with no apparent difference between the two groups. Other prognostic factors, such as histologic subtype, grade and hormone receptor status did not differ between the groups [see Clinical Studies (14.2)].

Consistent with the WHI clinical trial, observational studies have also reported an increased risk of breast cancer for estrogen plus progestin therapy, and a smaller increased risk for estrogen-alone therapy, after several years of use. The risk increased with duration of use, and appeared to return to baseline over about 5 years after stopping treatment (only the observational studies have substantial data on risk after stopping). Observational studies also suggest that the risk of breast cancer was greater, and became apparent earlier, with estrogen plus progestin therapy as compared to estrogen-alone therapy. However, these studies have not generally found significant variation in the risk of breast cancer among different estrogen plus progestin combinations, doses, or routes of administration.

The use of estrogen-alone and estrogen plus progestin has been reported to result in an increase in abnormal mammograms requiring further evaluation.

All women should receive yearly breast examinations by a healthcare provider and perform monthly breast self-examinations. In addition, mammography examinations should be scheduled based on patient age, risk factors, and prior mammogram results.

Ovarian Cancer

The WHI estrogen plus progestin substudy reported a statistically non-significant increased risk of ovarian cancer. After an average follow-up of 5.6 years, the relative risk for ovarian cancer for CE plus MPA versus placebo was 1.58 (95 percent nCI, 0.77-3.24). The absolute risk for CE plus MPA versus placebo was 4 versus 3 cases per 10,000 women-years.^7 In some epidemiologic studies, the use of estrogen-only products, in particular for 5 or more years, has been associated with an increased risk of ovarian cancer. However, the duration of exposure associated with increased risk is not consistent across all epidemiologic studies, and some report no association.

5.4 Probable Dementia

In the estrogen-alone Women’s Health Initiative Memory Study (WHIMS), an ancillary study of WHI, a population of 2,947 hysterectomized women aged 65 to 79 years was randomized to daily CE (0.625 mg) or placebo.

In the WHIMS estrogen-alone ancillary study, after an average follow-up of 5.2 years, 28 women in the estrogen-alone group and 19 women in the placebo group were diagnosed with probable dementia. The relative risk of probable dementia for CE-alone versus placebo was 1.49 (95 percent nCI, 0.83-2.66). The absolute risk of probable dementia for CE alone versus placebo was 37 versus 25 cases per 10,000 women-years^8 [see Use in Specific Populations (8.5), and Clinical Studies (14.3)].

In the WHIMS estrogen plus progestin ancillary study, a population of 4,532 postmenopausal women 65 to 79 years of age was randomized to daily CE (0.625 mg) plus MPA (2.5 mg) or placebo. After an average follow-up of 4 years, 40 women in the CE plus MPA group and 21 women in the placebo group were diagnosed with probable dementia. The relative risk of probable dementia for CE plus MPA versus placebo was 2.05 (95 percent nCI, 1.21-3.48). The absolute risk of probable dementia for CE plus MPA versus placebo was 45 versus 22 cases per 10,000 women-years^8 [see Use in Specific Populations (8.5), and Clinical Studies (14.3)].

When data from the two populations in the WHIMS estrogen-alone and estrogen plus progestin ancillary studies were pooled as planned in the WHIMS protocol, the reported overall relative risk for probable dementia was 1.76 (95 percent nCI, 1.19-2.60). Since both substudies were conducted in women aged 65 to 79 years, it is unknown whether these findings apply to younger postmenopausal women^8 [see Use in Specific Populations (8.5), and Clinical Studies (14.3)].

5.5 Gallbladder Disease

A 2- to 4-fold increase in the risk of gallbladder disease requiring surgery in postmenopausal women receiving estrogens has been reported.

5.6 Hypercalcemia

Estrogen administration may lead to severe hypercalcemia in women with breast cancer and bone metastases. If hypercalcemia occurs, use of the drug should be stopped and appropriate measures taken to reduce the serum calcium level.

5.7 Visual Abnormalities

Retinal vascular thrombosis has been reported in women receiving estrogens. Discontinue medication pending examination if there is a sudden partial or complete loss of vision, or a sudden onset of proptosis, diplopia, or migraine. If examination reveals papilledema or retinal vascular lesions, estrogens should be permanently discontinued.

5.8 Addition of a Progestin When a Woman Has Not Had a Hysterectomy

Studies of the addition of a progestin for 10 or more days of a cycle of estrogen administration or daily with estrogen in a continuous regimen have reported a lowered incidence of endometrial hyperplasia than would be induced by estrogen treatment alone. Endometrial hyperplasia may be a precursor to endometrial cancer.

There are, however, possible risks that may be associated with the use of progestins with estrogens compared to estrogen-alone regimens. These include an increased risk of breast cancer.

5.9 Elevated Blood Pressure

In a small number of case reports, substantial increases in blood pressure have been attributed to idiosyncratic reactions to estrogens. In a large, randomized, placebo-controlled clinical trial, a generalized effect of estrogens on blood pressure was not seen.

5.10 Hypertriglyceridemia

In women with preexisting hypertriglyceridemia, estrogen therapy may be associated with elevations of plasma triglycerides leading to pancreatitis. Consider discontinuation of treatment if pancreatitis occurs.

5.11 Hepatic Impairment and/or Past History of Cholestatic Jaundice

Estrogens may be poorly metabolized in women with impaired liver function. For women with a history of cholestatic jaundice associated with past estrogen use or with pregnancy, caution should be exercised, and in the case of recurrence, medication should be discontinued.

5.12 Hypothyroidism

Estrogen administration leads to increased thyroid-binding globulin (TBG) levels. Women with normal thyroid function can compensate for the increased TBG by making more thyroid hormone, thus maintaining free T4 and T3 serum concentrations in the normal range. Women dependent on thyroid hormone replacement therapy who are also receiving estrogens may require increased doses of their thyroid replacement therapy. These women should have their thyroid function monitored in order to maintain their free thyroid hormone levels in an acceptable range.

5.13 Fluid Retention

Estrogens may cause some degree of fluid retention. Women with conditions that might be influenced by this factor, such as a cardiac or renal dysfunction, warrant careful observation when estrogens are prescribed.

5.14 Hypocalcemia

Estrogen therapy should be used with caution in women with hypoparathyroidism as estrogen-induced hypocalcemia may occur.

5.15 Exacerbation of Endometriosis

A few cases of malignant transformation of residual endometrial implants have been reported in women treated post-hysterectomy with estrogen-alone therapy. For women known to have residual endometriosis post-hysterectomy, the addition of progestin should be considered.

5.16 Exacerbation of Other Conditions

Estrogen therapy may cause an exacerbation of asthma, diabetes mellitus, epilepsy, migraine, porphyria, systemic lupus erythematosus, and hepatic hemangiomas and should be used with caution in women with these conditions.

5.17 Local Abrasion

A few cases of local abrasion induced by the Vagifem applicator have been reported, especially in women with severely atrophic vaginal mucosa.

5.18 Laboratory Tests

Serum follicle stimulating hormone and estradiol levels have not been shown to be useful in the management of moderate to severe symptoms of vulvar and vaginal atrophy.

5.19 Drug/Laboratory Test Interactions

Accelerated prothrombin time, partial thromboplastin time, and platelet aggregation time; increased platelet count; increased factors II, VII antigen, VIII antigen, VIII coagulant activity, IX, X, XII, VII-X complex, II-VII-X complex, and beta-thromboglobulin; decreased levels of antifactor Xa and antithrombin III, decreased antithrombin III activity; increased levels of fibrinogen and fibrinogen activity; increased plasminogen antigen and activity.

Increased thyroid-binding globulin (TBG) levels leading to increased circulating total thyroid hormone as measured by protein-bound iodine (PBI), T4 levels (by column or by radioimmunoassay) or T3 levels by radioimmunoassay. T3 resin uptake is decreased, reflecting the elevated TBG. Free T4 and free T3 concentrations are unaltered. Women on thyroid replacement therapy may require higher doses of thyroid hormone.

Other binding proteins may be elevated in serum, for example, corticosteroid binding globulin (CBG), sex hormone-binding globulin (SHBG), leading to increased total circulating corticosteroids and sex steroids, respectively. Free hormone concentrations, such as testosterone and estradiol, may be decreased. Other plasma proteins may be increased (angiotensinogen/renin substrate, alpha-1-antitrypsin, ceruloplasmin).

Increased plasma HDL and HDL2 cholesterol subfraction concentrations, reduced LDL cholesterol concentrations, increased triglyceride levels.

Impaired glucose tolerance.

6 ADVERSE REACTIONS

The following serious adverse reactions are discussed elsewhere in the labeling:

- Cardiovascular Disorders [see Boxed Warning, Warnings and Precautions (5.2)]
- Endometrial Cancer [see Boxed Warning, Warnings and Precautions (5.3)]

6.1 Clinical Study Experience

Because clinical trials are conducted under widely varying conditions, adverse reaction rates observed in the clinical trial of a drug cannot be directly compared to rates in the clinical trials of another drug and may not reflect the rates observed in practice.

In a 12-month randomized, double-blind, parallel group, placebo-controlled study, a total of 309 postmenopausal women were randomized to receive either placebo or Vagifem 10 mcg tablets. Adverse events with an incidence of ≥5% in the Vagifem 10 mcg group and greater than those reported in the placebo group are listed in Table 1.

Table 1: Treatment-Emergent Adverse Events Reported at a Frequency of ≥5% and More Frequent in Women Receiving Vagifem 10 mcg
Body System; Adverse Event | Treatment; Number (%) of Women
 | Placebo; N = 103; n (%) | Vagifem; N = 205; n (%)
Body As A Whole
Back Pain | 2 (2) | 14(7)
Digestive System
Diarrhea | 0 | 11 (5)
Urogenital System
Vulvovaginal Mycotic Infection | 3 (3) | 17 (8)
Vulvovaginal Pruritis | 2 (2) | 16 (8)
N = Total number of women in study.
n = Number of women who experienced adverse event.

In a 12-week, randomized, double-blind, placebo-controlled study, 138 postmenopausal women were randomized to receive either placebo or Vagifem 25 mcg tablets. Adverse events with an incidence of ≥5% in the Vagifem 25 mcg group and greater than those reported in the placebo group are listed in Table 2.

Table 2: Treatment-Emergent Adverse Events Reported at a Frequency of ≥5% and More Frequent in Women Receiving Vagifem 25 mcg
Body System; Adverse Event | Treatment; Number (%) of Women
 | Placebo; N = 47; n (%) | Vagifem; N = 91; n (%)
Body As A Whole
Headache | 3 (6) | 8 (9)
Abdominal Pain | 2 (4) | 6 (7)
Back Pain | 3 (6) | 6 (7)
Respiratory System
Upper Respiratory Tract; Infection | 2 (4) | 5 (5)
Urogenital System
Moniliasis Genital | 1 (2) | 5 (5)
N = Total number of women in study.
n = Number of women who experienced adverse event.

6.2 Postmarketing Experience

The following adverse reactions have been reported during post approval use of Vagifem 25 mcg. Because these reactions are reported voluntarily from a population of uncertain size, it is not always possible to reliably estimate their frequency or establish a causal relationship to drug exposure.

Genitourinary System

Endometrial cancer, endometrial hyperplasia, vaginal irritation, vaginal pain, vaginismus, vaginal ulceration

Breast

Breast cancer

Cardiovascular

Deep vein thrombosis

Gastrointestinal

Diarrhea

Skin

Urticaria, erythematous/pruritic rash, genital pruritus

Central Nervous System

Aggravated migraine, depression, insomnia

Miscellaneous

Fluid retention, weight increase, drug ineffectiveness, hypersensitivity, blood estrogen increase

Additional postmarketing adverse reactions have been reported in patients receiving other forms of hormone therapy.

7 DRUG INTERACTIONS

No drug- drug interaction studies have been conducted with Vagifem.

7.1 Metabolic Interactions

In-vitro and in-vivo studies have shown that estrogens are metabolized partially by cytochrome P450 3A4 (CYP3A4). Therefore, inducers or inhibitors of CYP3A4 may affect estrogen drug metabolism. Inducers of CYP3A4, such as St. John's Wort (Hypericum perforatum) preparations, phenobarbital, carbamazepine, and rifampin, may reduce plasma concentrations of estrogens, possibly resulting in a decrease in therapeutic effects and/or changes in the uterine bleeding profile. Inhibitors of CYP3A4 such as erythromycin, clarithromycin, ketoconazole, itraconazole, ritonavir and grapefruit juice may increase plasma concentrations of estrogens and may result in side effects.

8 USE IN SPECIFIC POPULATIONS

8.1 Pregnancy

Vagifem should not be used during pregnancy [see Contraindications (4)]. There appears to be little or no increased risk of birth defects in children born to women who have used estrogens and progestins as an oral contraceptive inadvertently during early pregnancy.

8.3 Nursing Mothers

Vagifem should not be used during lactation. Estrogen administration to nursing women has been shown to decrease the quantity and quality of breast milk. Detectable amounts of estrogens have been identified in the breast milk of women receiving estrogen. Caution should be exercised when Vagifem is administered to a nursing woman.

8.4 Pediatric Use

Vagifem is not indicated in children. Clinical studies have not been conducted in the pediatric population.

8.5 Geriatric Use

There have not been sufficient numbers of geriatric women involved in clinical studies utilizing Vagifem to determine whether those over 65 years of age differ from younger subjects in their response to Vagifem.

The Women’s Health Initiative Study

In the Women’s Health Initiative (WHI) estrogen-alone substudy (daily conjugated estrogens 0.625 mg versus placebo), there was a higher relative risk of stroke in women greater than 65 years of age [see Clinical Studies (14.2)].

In the WHI estrogen plus progestin substudy, there was a higher relative risk of nonfatal stroke and invasive breast cancer in women greater than 65 years of age [see Clinical Studies (14.2)].

The Women’s Health Initiative Memory Study

In the Women’s Health Initiative Memory Study (WHIMS) of postmenopausal women 65 to 79 years of age, there was an increased risk of developing probable dementia in the estrogen-alone and the estrogen plus progestin substudies when compared to placebo [see Clinical Studies (14.3)].

Since both ancillary studies were conducted in women 65 to 79 years of age, it is unknown whether these findings apply to younger postmenopausal women^8 [see Clinical Studies (14.3)].

8.6 Renal Impairment

The effect of renal impairment on the pharmacokinetics of Vagifem has not been studied.

8.7 Hepatic Impairment

The effect of hepatic impairment on the pharmacokinetics of Vagifem has not been studied.

10 OVERDOSAGE

Overdosage of estrogen may cause nausea and vomiting, breast tenderness, dizziness, abdominal pain, drowsiness/fatigue and withdrawal bleeding in women. Treatment of overdose consists of discontinuation of Vagifem together with institution of appropriate symptomatic care.

11 DESCRIPTION

Vagifem 10 mcg (estradiol vaginal tablets) are small, white, film-coated tablets containing 10.3 mcg of estradiol hemihydrate equivalent to 10 mcg of estradiol. Vagifem 25 mcg (estradiol vaginal tablets) are small, white, film-coated tablets containing 25.8 mcg of estradiol hemihydrate equivalent to 25 mcg of estradiol. Each tablet of Vagifem 10 mcg and 25 mcg contains the following excipients: hypromellose, lactose monohydrate, maize starch and magnesium stearate. The film coating contains hypromellose and polyethylene glycol. Each Vagifem tablet is 6 mm in diameter and is placed in a disposable applicator. Each tablet-filled applicator is packaged separately in a blister pack. Vagifem tablets are used intravaginally. When the tablet comes in contact with the vaginal mucosa, estradiol is released into the vagina.

Estradiol hemihydrate is a white, almost white or colorless crystalline solid, chemically described as estra-1,3,5 (10)-triene-3,17β-diol. The chemical formula is C18H24O2 • ½ H2O with a molecular weight of 281.4.

The structural formula is:

12 CLINICAL PHARMACOLOGY

12.1 Mechanism of Action

Endogenous estrogens are largely responsible for the development and maintenance of the female reproductive system and secondary sexual characteristics. Although circulating estrogens exist in a dynamic equilibrium of metabolic interconversions, estradiol is the principal intracellular human estrogen and is substantially more potent than its metabolites, estrone and estriol, at the receptor level.

The primary source of estrogen in normally cycling adult women is the ovarian follicle, which secretes 70 to 500 mcg of estradiol daily, depending on the phase of the menstrual cycle. After menopause, most endogenous estrogen is produced by conversion of androstenedione, secreted by the adrenal cortex, to estrone by peripheral tissues. Thus, estrone and the sulfate conjugated form, estrone sulfate, are the most abundant circulating estrogens in postmenopausal women.

Estrogens act through binding to nuclear receptors in estrogen-responsive tissues. To date, two estrogen receptors have been identified. These vary in proportion from tissue to tissue.

Circulating estrogens modulate the pituitary secretion of the gonadotropins, luteinizing hormone (LH), and follicle-stimulating hormone (FSH) through a negative feedback mechanism. Estrogens act to reduce the elevated levels of these hormones seen in postmenopausal women.

Estrogens act through binding to nuclear receptors in estrogen-responsive tissues. To date, two estrogen receptors have been identified. These vary in proportion from tissue to tissue.

Circulating estrogens modulate the pituitary secretion of the gonadotropins, luteinizing hormone (LH), and follicle-stimulating hormone (FSH) through a negative feedback mechanism. Estrogens act to reduce the elevated levels of these hormones seen in postmenopausal women.

12.2 Pharmacodynamics

Currently, there are no pharmacodynamic data known for Vagifem.

12.3 Pharmacokinetics

Absorption

Estrogen drug products are well absorbed through the skin, mucous membranes, and the gastrointestinal (GI) tract. The vaginal delivery of estrogens circumvents first-pass metabolism.

In a single-center, randomized, open-label, multiple-dose, parallel group study conducted in 58 patients, Vagifem 10 mcg and 25 mcg demonstrated a mean estradiol (E2) Cave at Day 83 of 5.5 pg/mL and 11.59 pg/mL, respectively after 12 weeks of treatment (see Tables 3 and 4).

Table 3: Arithmetic Means of Estradiol (E2), Estrone (E1), and Estrone Sulfate (E1S) PK Parameters Following Multiple Doses of Vagifem 10 mcg
Uncorrected for baseline, N=29
 | E2 |  |  | E1 |  |  | E1S
 | AUC0-24; (h.pg/mL) | Cave (0-24); (pg/mL) | %CV [CV: Coefficient of Variance for both AUC0-24 and Cave(0-24)] | AUC0-24; (h.pg/mL) | Cave (0-24); (pg/mL) | %CV | AUC0-24; (h.pg/mL) | Cave (0-24); (pg/mL) | %CV
Day 1 | 242.08 | 10.09 | 33.02 | 485.21 | 20.22 | 44.86 | 5158.32 | 214.93 | 53.57
Day 14 | 176.49 | 7.35 | 43.69 | 496.14 | 20.67 | 30.88 | 6323.41 | 263.48 | 50.07
Day 83 | 132.04 | 5.50 | 59.69 | 411.08 | 17.13 | 39.58 | 3804.65 | 158.53 | 49.76

Table 4: Arithmetic Means of Estradiol (E2), Estrone (E1), and Estrone Sulfate (E1S) PK Parameters Following Multiple Doses of Vagifem 25 mcg
Uncorrected for baseline, N=28 or 27
 | E2 |  |  | E1 |  |  | E1S
 | AUC0-24; (h.pg/mL) | Cave (0-24); (pg/mL) | %CV [CV: Coefficient of Variance for both AUC0-24 and Cave(0-24)] | AUC0-24; (h.pg/mL) | Cave (0-24); (pg/mL) | %CV | AUC0-24; (h.pg/mL) | Cave (0-24); (pg/mL) | %CV
Day 1 | 495.27 | 20.64 | 25.70 | 567.07 | 23.63 | 28.96 | 5738.32 | 239.10 | 47.72
Day 14 | 466.63 | 19.44 | 33.53 | 662.94 | 27.62 | 24.36 | 7725.90 | 321.91 | 43.67
Day 83 | 278.27 | 11.59 | 61.83 | 500.06 | 20.84 | 34.99 | 4110.84 | 171.29 | 51.38

Distribution

The distribution of exogenous estrogens is similar to that of endogenous estrogens. Estrogens are widely distributed in the body and are generally found in higher concentrations in the sex hormone target organs. Estrogens circulate in the blood largely bound to sex hormone binding globulin (SHBG) and albumin.

Metabolism

Exogenous estrogens are metabolized in the same manner as endogenous estrogens. Circulating estrogens exist in a dynamic equilibrium of metabolic interconversions. These transformations take place mainly in the liver. Estradiol is converted reversibly to estrone, and both can be converted to estriol, which is the major urinary metabolite. Estrogens also undergo enterohepatic recirculation via sulfate and glucuronide conjugation in the liver, biliary secretion of conjugates into the intestine, and hydrolysis in the gut followed by reabsorption. In postmenopausal women, a significant portion of the circulating estrogens exist as sulfate conjugates, especially estrone sulfate, which serves as a circulating reservoir for the formation of more active estrogens.

Excretion

Estradiol, estrone, and estriol are excreted in the urine along with glucuronide and sulfate conjugates.

Use in Specific Populations

Geriatric Use: There have not been sufficient numbers of geriatric women involved in clinical studies utilizing Vagifem to determine whether those over 65 years of age differ from younger subjects in their response to Vagifem.

Renal Impairment: The effect of renal impairment on the pharmacokinetics of Vagifem has not been studied.

Hepatic Impairment: The effect of hepatic impairment on the pharmacokinetics of Vagifem has not been studied.

Drug Interactions

In-vitro and in-vivo studies have shown that estrogens are metabolized partially by CYP3A4. Therefore, inducers or inhibitors of CYP3A4 may affect estrogen drug metabolism. Inducers of CYP3A4, such as St. John's Wort (Hypericum perforatum) preparations, phenobarbital, carbamazepine, and rifampin, may reduce plasma concentrations of estrogens, possibly resulting in a decrease in therapeutic effects and/or changes in the uterine bleeding profile. Inhibitors of CYP3A4 such as erythromycin, clarithromycin, ketoconazole, itraconazole, ritonavir and grapefruit juice may increase plasma concentrations of estrogens and may result in side effects.

13 NONCLINICAL TOXICOLOGY

13.1 Carcinogenesis, Mutagenesis, Impairment of Fertility

Long-term continuous administration of natural and synthetic estrogens in certain animal species increases the frequency of carcinomas of the breast, uterus, cervix, vagina, testis, and liver.

14 CLINICAL STUDIES

14.1 Effects on Vaginal Atrophy

Vagifem 10 mcg

A 12-month double-blind, randomized, parallel group, placebo-controlled multicenter study was conducted in the U.S. and Canada to evaluate the efficacy and safety of Vagifem 10 mcg in the treatment of atrophic vaginitis in 309 postmenopausal women between 46 and 81 years of age (mean age = 57.6 years) who at baseline identified their most bothersome symptom of atrophic vaginitis from among six symptoms (vaginal dryness, vaginal and/or vulvar irritation/itching, vaginal soreness, dysuria, dyspareunia and vaginal bleeding associated with intercourse). Women inserted one tablet intravaginally each day for 14 days, then one tablet twice weekly for the remaining 50 weeks. The majority (92.9%) of the women were Caucasian (n=287), 3.2% were Black (n=10), 1.6% were Asian (n=5) and 2.2% were Other (n=7). All subjects were assessed for improvement in the mean change from baseline to Week 12 for co-primary efficacy variables of: a composite of most bothersome symptoms of atrophic vaginitis; percentage of vaginal superficial cells and percentage of vaginal parabasal cells on a vaginal smear; and vaginal pH.

Relief of Vaginal Symptoms

Vagifem 10 mcg was statistically superior to placebo in reducing the severity of a composite score of most bothersome symptoms associated with atrophic vaginitis at Week 12 (see Table 5).

Table 5: Mean Change from Baseline to Week 12 in a Composite Score of Most Bothersome Symptoms Compared to Placebo – ITT Population [All randomized subjects who received at least one dose of study drug and had at least one post-baseline evaluation.]
 | Placebo | Vagifem 10 mcg
ITT Population
N | 93 | 190
Baseline mean; composite score | 2.29 | 2.35
Change from baseline at Week 12 (LOCF) | -0.84 | -1.20
p-value versus Placebo | --- | 0.002

Also demonstrated for Vagifem 10 mcg compared to placebo was a statistically significant increase in the percentage of superficial cells at Week 12 (13.2 percent compared to 3.8 percent for matching placebo, p<0.001), a statistically significant decrease in parabasal cells at Week 12 (-37.0 percent compared to -9.3 percent for matching placebo, p<0.001), and a statistically significant mean reduction between baseline and Week 12 in vaginal pH score (-1.3 compared to -0.4 for matching placebo, p<0.001).

Endometrial safety was assessed by endometrial biopsy at the screening and final study visit. Of the 172 subjects in the Vagifem 10 mcg group who had a biopsy performed at end of study, 92 subjects had endometrial tissue that was atrophic or inactive and 73 subjects had no tissue or tissue insufficient for diagnosis. There was one case of adenocarcinoma grade 2 and one case of complex hyperplasia without atypia. Three subjects exhibited polyps (two atrophic polyps and one adenomyomatus type polyp) and two others had adenomyosis and an atypical epithelial proliferation.

Endometrial safety of Vagifem 10 mcg was additionally evaluated in a second, 12 month, open-label, multicenter safety study. Of the 297 subjects who had a biopsy performed at end of study, 183 subjects had endometrial tissue that was atrophic or inactive and 111 subjects had no tissue or tissue insufficient for diagnosis. There was one case of complex hyperplasia without atypia. Two subjects exhibited polyps.

Vagifem 25 mcg

A placebo-controlled comparison study was done in the U.S., in which 230 women were randomized to receive either placebo, Vagifem 25 mcg or 10 mcg estradiol vaginal tablets. Women inserted one tablet intravaginally each day for 14 days, then one tablet twice weekly for the remaining 10 weeks. All subjects were assessed for vaginal symptoms. Vagifem 25 mcg was superior to placebo in reducing the severity of a composite score of symptoms associated with atrophic vaginitis (see Table 6).

An open-label, controlled comparison study was done in Canada in which 159 women were randomized to receive either Vagifem 25 mcg or a comparator drug. Two (2) grams of the comparator drug was given daily for 3 weeks, withheld for 1 week, then repeated cyclically (3 weeks on, 1 week off) for up to 24 weeks; Vagifem 25 mcg was administered daily for 2 weeks, then twice weekly for the remaining 22 weeks. In this study, subjects were assessed for relief of symptoms. Vagifem 25 mcg was equally effective as the approved comparator product at the 2.0 gm dose in the relief of symptoms.

Table 6: Mean Change from Baseline to Week 7 and Week 12 in a Composite Score of Symptoms Compared to Placebo – ITT Population [All randomized subjects who received at least one dose of study drug and had at least one post-baseline evaluation.]
 | Placebo | Vagifem 25 mcg
ITT Population
N | 47 | 91
Baseline mean | 1.93 | 1.85
Change from baseline at Week 7 (LOCF) | -0.85 | -1.22
Change from baseline at Week 12 (LOCF) | -0.83 | -1.33
p-value versus Placebo – Week 7 (LOCF) | --- | 0.016
p-value versus Placebo – Week 12 (LOCF) | --- | 0.005

In the placebo-controlled study endometrial biopsies in non-hysterectomized women at week 12 were performed on 86 subjects (Vagifem 25 mcg: 32 subjects, estradiol 10 mcg: 33 subjects, Placebo: 21 subjects). Of these, 3 subjects each from the Vagifem 25 mcg and placebo groups and 8 from the 10 mcg estradiol group had insufficient tissue samples. Among those with biopsies that yielded sufficient tissue, results were normal with the exception of one subject in the Vagifem 25 mcg group, who had a simple hyperplasia without atypia.

In the open-label study comparing Vagifem 25 mcg with a comparator vaginal cream on 49 women in each treatment group, endometrial biopsies were obtained at the screening visit and at the end of treatment. At the end of the study (Week 24), all subjects in the Vagifem treatment group whose biopsies yielded sufficient tissue showed an atrophic endometrium with the exception of one subject who had a proliferative endometrium.

14.2 Women’s Health Initiative Studies

The Women’s Health Initiative (WHI) enrolled approximately 27,000 predominantly healthy postmenopausal women in two substudies to assess the risks and benefits of either the use of daily oral CE (0.625 mg)-alone or in combination with MPA (2.5 mg) compared to placebo in the prevention of certain chronic diseases. The primary endpoint was the incidence of coronary heart disease [(CHD) defined as nonfatal myocardial infarction (MI), silent MI and CHD death], with invasive breast cancer as the primary adverse outcome studied. A “global index” included the earliest occurrence of CHD, invasive breast cancer, stroke, pulmonary embolism (PE), endometrial cancer (only in the CE plus MPA substudy), colorectal cancer, hip fracture, or death due to other causes. These substudies did not evaluate the effects of CE or CE plus MPA on menopausal symptoms.

WHI Estrogen-Alone Substudy

The WHI estrogen-alone substudy was stopped early because an increased risk of stroke was observed, and it was deemed that no further information would be obtained regarding the risks and benefits of estrogen alone in predetermined primary endpoints.

Results of the estrogen-alone substudy, which included 10,739 women (average age of 63 years, range 50 to 79; 75.3 percent White, 15.1 percent Black, 6.1 percent Hispanic, 3.6 percent Other) after an average follow-up of 7.1 years, are presented in Table 7.

Table 7: Relative and Absolute Risk Seen in the Estrogen-Alone Substudy of WHI
Event | Relative Risk; CE vs. Placebo; (95% nCI) | CE; n=5,310 | Placebo; n=5,429
 |  | Absolute Risk per 10,000 Women-Years
CHD events [Results are based on centrally adjudicated data for an average follow-up of 7.1 years.]; Non-fatal MI; CHD death | 0.95 (0.78-1.16); 0.91 (0.73-1.14); 1.01 (0.71-1.43) | 54; 40; 16 | 57; 43; 16
All Stroke | 1.33 (1.05-1.68) | 45 | 33
Ischemic | 1.55 (1.19-2.01) | 38 | 25
Deep vein thrombosis , [Not included in "global index".] | 1.47 (1.06-2.06) | 23 | 15
Pulmonary embolism | 1.37 (0.90-2.07) | 14 | 10
Invasive breast cancer | 0.80 (0.62-1.04) | 28 | 34
Colorectal cancer [Results are based on an average follow-up of 6.8 years.] | 1.08 (0.75-1.55) | 17 | 16
Hip fracture | 0.65 (0.45-0.94) | 12 | 19
Vertebral fractures , | 0.64 (0.44-0.93) | 11 | 18
Lower arm/wrist fractures,, | 0.58 (0.47-0.72) | 35 | 59
Total fractures , | 0.71 (0.64-0.80) | 144 | 197
Death due to other causes, , | 1.08 (0.88-1.32) | 53 | 50
Overall mortality, | 1.04 (0.88-1.22) | 79 | 75
Global Index | 1.02 (0.92-1.13) | 206 | 201

For those outcomes included in the WHI “global index” that reached statistical significance, the absolute excess risk per 10,000 women-years in the group treated with CE-alone was 12 more strokes while the absolute risk reduction per 10,000 women-years was 7 fewer hip fractures.^9 The absolute excess risk of events included in the “global index” was a non-significant 5 events per 10,000 women-years. There was no difference between the groups in terms of all-cause mortality [see Boxed Warnings, and Warnings and Precautions(5)].

No overall difference for primary CHD events (nonfatal MI, silent MI and CHD death) and invasive breast cancer incidence in women receiving CE-alone compared with placebo was reported in final centrally adjudicated results from the estrogen-alone substudy, after an average follow up of 7.1 years.

Centrally adjudicated results for stroke events from the estrogen-alone substudy, after an average follow-up of 7.1 years, reported no significant difference in distribution of stroke subtype or severity, including fatal strokes, in women receiving CE-alone compared to placebo. Estrogen-alone increased the risk for ischemic stroke, and this excess risk was present in all subgroups of women examined, see Table 7.^10

Timing of the initiation of estrogen therapy relative to the start of menopause may affect the overall risk benefit profile. The WHI estrogen-alone substudy stratified by age showed in women 50-59 years of age, a non-significant trend toward reduced risk for CHD [HR 0.63 (95 percent CI 0.36-1.09)] and overall mortality [HR 0.71 (95 percent CI, 0.46-1.11)].

WHI Estrogen Plus Progestin Substudy

The WHI estrogen plus progestin substudy was stopped early. According to the predefined stopping rule, after an average follow-up of 5.6 years of treatment, the increased risk of breast cancer and cardiovascular events exceeded the specified benefits included in the “global index.” The absolute excess risk of events included in the “global index” was 19 per 10,000 women-years.

For those outcomes included in the WHI “global index” that reached statistical significance after 5.6 years of follow-up, the absolute excess risks per 10,000 women-years in the group treated with CE plus MPA were 7 more CHD events, 8 more strokes, 10 more PEs, and 8 more invasive breastcancers, while the absolute risk reductions per 10,000 women-years were 6 fewer colorectal cancers and 5 fewer hip fractures.

Results of the estrogen plus progestin substudy, which included 16,608 women (average 63 years of age, range 50 to 79; 83.9 percent White, 6.8 percent Black, 5.4 percent Hispanic, 3.9 percent Other) are presented in Table 8. These results reflect centrally adjudicated data after an average follow-up of 5.6 years.

Table 8: Relative and Absolute Risk Seen in the Estrogen Plus Progestin Substudy of WHI at an Average of 5.6 Years,
Event | Relative Risk; CE/MPA vs Placebo; (95% nCI) | CE/MPA; n=8,506 | Placebo; n=8,102
 |  | Absolute Risk per 10,000 Women-Years
CHD events; Non-fatal MI; CHD death | 1.23 (0.99-1.53); 1.28 (1.00-1.63); 1.10 (0.70-1.75) | 41; 31; 8 | 34; 25; 8
All strokes; Ischemic stroke | 1.31 (1.02-1.68); 1.44 (1.09-1.90) | 33; 26 | 25; 18
Deep vein thrombosis [Not included in “global index”.] | 1.95 (1.43-2.67) | 26 | 13
Pulmonary embolism | 2.13 (1.45-3.11) | 18 | 8
Invasive breast cancer | 1.24 (1.01-1.54) | 41 | 33
Colorectal cancer | 0.61 (0.42-0.87) | 10 | 16
Endometrial cancer | 0.81 (0.48-1.36) | 6 | 7
Cervical cancer | 1.44 (0.47-4.42) | 2 | 1
Hip fracture | 0.67 (0.47-0.96) | 11 | 16
Vertebral fractures | 0.65 (0.46-0.92) | 11 | 17
Lower arm/wrist fractures | 0.71 (0.59-0.85) | 44 | 62
Total fractures | 0.76 (0.69-0.83) | 152 | 199
Overall Mortality | 1.00 (0.83-1.19) | 52 | 52
Global Index | 1.13 (1.02-1.25) | 184 | 165

Timing of the initiation of estrogen therapy relative to the start of menopause may affect the overall risk benefit profile. The WHI estrogen plus progestin substudy stratified by age showed in women 50-59 years of age, a non-significant trend toward reduced risk for overall mortality [HR 0.69 (95 percent CI, 0.44-1.07)].

14.3 Women’s Health Initiative Memory Study

The estrogen-alone Women’s Health Initiative Memory Study (WHIMS), an ancillary study of WHI, enrolled 2,947 predominately healthy hysterectomized postmenopausal women 65 to 79 years of age and older (45 percent were 65 to 69 years of age; 36 percent were 70 to 74 years of age; 19 percent were 75 years of age and older) to evaluate the effects of daily CE (0.625 mg) on the incidence of probable dementia (primary outcome) compared to placebo.

After an average follow-up of 5.2 years, the relative risk of probable dementia for CE-alone versus placebo was 1.49 (95 percent CI, 0.83 - 2.66).

The absolute risk of probable dementia for CE-alone versus placebo was 37 versus 25 cases per 10,000 women-years. Probable dementia as defined in this study included Alzheimer's disease (AD), vascular dementia (VaD) and mixed types (having features of both AD and VaD). The most common classification of probable dementia in both the treatment and placebo groups was AD. Since the ancillary study was conducted in women 65 to 79 years of age, it is unknown whether these findings apply to younger postmenopausal women [see Warnings and Precautions (5.4), and Use in Specific Populations (8.5)].

The WHIMS estrogen plus progestin substudy enrolled 4,532 predominantly healthy postmenopausal women 65 years of age and older (47 percent were 65 to 69 years of age; 35 percent were 70 to 74 years; 18 percent were 75 years of age and older) to evaluate the effects of daily CE (0.625 mg) plus MPA (2.5 mg) on the incidence of probable dementia (primary outcome) compared to placebo.

After an average follow-up of 4 years, the relative risk of probable dementia for CE (0.625 mg) plus MPA (2.5 mg) versus placebo was 2.05 (95 percent CI, 1.21-3.48). The absolute risk of probable dementia for CE (0.625 mg) plus MPA (2.5 mg) versus placebo was 45 versus 22 per 10,000 women-years. Probable dementia as defined in this study included AD, VaD and mixed types (having features of both AD and VaD). The most common classification of probable dementia in both the treatment and placebo groups was AD. Since the ancillary study was conducted in women 65 to 79 years of age, it is unknown whether these findings apply to younger postmenopausal women [see Warnings and Precautions (5.4), and Use in Specific Populations (8.5)].

When data from the two populations were pooled as planned in the WHIMS protocol, the reported overall relative risk for probable dementia was 1.76 (95 percent CI, 1.19-2.60). Differences between groups became apparent in the first year of treatment. It is unknown whether these findings apply to younger postmenopausal women [see Warnings and Precautions (5.4), and Use in Specific Populations (8.5)].

15 REFERENCES

1. Rossouw JE, et al. Postmenopausal Hormone Therapy and Risk of Cardiovascular Disease by Age and Years Since Menopause. JAMA. 2007; 297:1465-1477.
2. Hsia J, et al. Conjugated Equine Estrogens and Coronary Heart Disease. Arch Int Med. 2006; 166:357-365.
3. Curb JD, et al. Venous Thrombosis and Conjugated Equine Estrogen in Women Without a Uterus. Arch Int Med. 2006; 166:772-780.
4. Cushman M, et al. Estrogen Plus Progestin and Risk of Venous Thrombosis. JAMA. 2004; 292:1573-1580.
5. Stefanick ML, et al. Effects of Conjugated Equine Estrogens on Breast Cancer and Mammography Screening in Postmenopausal Women With Hysterectomy. JAMA. 2006; 295:1647-1657.
6. Chlebowski RT, et al. Influence of Estrogen Plus Progestin on Breast Cancer and Mammography in Healthy Postmenopausal Women. JAMA. 2003; 289:3234-3253.
7. Anderson GL, et al. Effects of Estrogen Plus Progestin on Gynecologic cancers and Associated Diagnostic Procedures. JAMA. 2003; 290:1739-1748.
8. Shumaker SA, et al. Conjugated Equine Estrogens and Incidence of Probable Dementia and Mild Cognitive Impairment in Postmenopausal Women. JAMA. 2004; 291:2947-2958.
9. Jackson RD, et al. Effects of Conjugated Equine Estrogen on Risk of Fractures and BMD in Postmenopausal Women With Hysterectomy: Results From the Women's Health Initiative Randomized Trial. J Bone Miner Res. 2006; 21:817-828.
10. Hendrix SL, et al. Effects of Conjugated Equine Estrogen on Stroke in the Women's Health Initiative. Circulation. 2006; 113:2425-2434.

16 HOW SUPPLIED/STORAGE AND HANDLING

16.1 How Supplied

Each Vagifem (estradiol vaginal tablets), 10 mcg is contained in a disposable, single-use applicator, packaged in a blister pack. Cartons contain 8 or 18 applicators with inset tablets.

Vagifem 10 mcg

8 applicators: NDC 54868-6182-0

Keep out of reach of children

16.2 Storage and Handling

Store at 25ºC (77ºF), excursions permitted to 15ºC-30ºC (59ºF-86ºF). Do not refrigerate.

[See USP Controlled Room Temperature.]

17 PATIENT COUNSELING INFORMATION

[See Section 17.5 FDA-APPROVED PATIENT LABELING]

17.1 Vaginal Bleeding

Inform postmenopausal women of the importance of reporting vaginal bleeding to their healthcare provider as soon as possible [see Warnings and Precautions (5.3)].

17.2 Possible Serious Adverse Reactions with Estrogens

Inform postmenopausal women of possible serious adverse reactions of estrogen therapy including Cardiovascular Disorders, Malignant Neoplasms, and Probable Dementia [see Warnings and Precautions (5.2, 5.3, 5.4)].

17.3 Possible Less Serious But Common Adverse Reactions with Estrogens

Inform postmenopausal women of possible less serious but common adverse reactions of estrogen therapy such as headache, breast pain and tenderness, nausea and vomiting.

17.4 Instructions for Use of Applicator

Step 1: Tear off a single applicator.

Step 2: Separate the plastic wrap and remove the applicator from the plastic wrap as shown in Figure A.

Figure A

Step 3: Hold the applicator so that the finger of one hand can press the applicator plunger as shown in Figure B.

Figure B

Step 4: Next select the best position for vaginal insertion of Vagifem (estradiol vaginal tablets) that is most comfortable for you. See suggested reclining Figure C or standing Figure D position illustrated below:

Figure C
Figure D

Step 5: Using the other hand, guide the applicator gently and comfortably through the vaginal opening (see Figures C and D above). If the tablet has come out of the applicator prior to insertion, carefully put it back into the applicator for insertion. Please keep your hands clean while handling the tablet.

Step 6: The applicator should be inserted (without forcing) as far as comfortably possible, or until half of the applicator is inside your vagina, whichever is less.

Step 7: Once the tablet-filled applicator has been inserted, gently press the plunger until the plunger is fully depressed. This will eject the tablet inside your vagina where it will dissolve slowly over several hours.

Step 8: After depressing the plunger, gently remove the applicator and dispose of it the same way you would a plastic tampon applicator. The applicator is of no further use and should be discarded properly. Insertion may be done at any time of the day. It is advisable to use the same time daily for all applications of Vagifem (estradiol vaginal tablets). If you have any questions, please consult your healthcare provider or pharmacist.

17.5 FDA-Approved Patient Labeling

Vagifem® (estradiol vaginal tablets)

Read this PATIENT INFORMATION before you start using Vagifem and read the patient information each time you refill your Vagifem prescription. There may be new information. This information does not take the place of talking to your healthcare provider about your menopausal symptoms and their treatment.

BOXED WARNING

What is the most important information I should know about VAGIFEM

(an estrogen hormone)

- Using estrogen-alone may increase your chance of getting cancer of the uterus (womb)

Report any unusual vaginal bleeding right away while you are using Vagifem. Vaginal bleeding after menopause may be a warning sign of cancer of the uterus (womb). Your healthcare provider should check any unusual vaginal bleeding to find the cause.

- Do not use estrogen-alone to prevent heart disease, heart attacks, strokes or dementia (decline of brain function)
- Using estrogen-alone may increase your chances of getting strokes or blood clots
- Using estrogen-alone may increase your chance of getting dementia, based on a study of women age 65 years or older
- Do not use estrogens with progestins to prevent heart disease, heart attack, or dementia
- Using estrogens with progestins may increase your chances of getting heart attacks, strokes, breast cancer, or blood clots
- Using estrogens with progestin may increase your chance of getting dementia, based on a study of women 65 years and older
- You and your healthcare provider should talk regularly about whether you still need treatment with Vagifem

What is Vagifem?

Vagifem is a medicine that contains estradiol (an estrogen hormone) in a vaginal tablet.

What is Vagifem used for?

Vagifem is used after menopause to:

- Treat menopausal changes in and around the vagina

You and your healthcare provider should talk regularly about whether you still need treatment with Vagifem to control these problems.

Who should not use Vagifem?

Do not start using Vagifem if you:

- Have unusual vaginal bleeding

- Currently have or have had certain cancers

Estrogens may increase the chances of getting certain types of cancers, including cancer of the breast or uterus. If you have, have had or suspect cancer, talk with your healthcare provider about whether you should use Vagifem.

- Had a stroke or heart attack

- Currently have or have had blood clots

- Currently have or have had liver problems

- Are allergic to Vagifem or any of its ingredients

See the list of ingredients in Vagifem at the end of this leaflet.

- Think you may be pregnant

Tell your health care provider:

- If you have any unusual vaginal bleeding

Vaginal bleeding after menopause may be a warning sign of cancer of the uterus (womb). Your healthcare provider should check any unusual vaginal bleeding to find the cause.

- About all of your medical problems

Your healthcare provider may need to check you more carefully if you have certain conditions, such as asthma (wheezing), epilepsy (seizures), diabetes, migraine, endometriosis, lupus, problems with your heart, liver, thyroid, kidneys, or have high calcium levels in your blood.

- About all the medicines you take

This includes prescription and nonprescription medicines, vitamins, and herbal supplements. Some medicines may affect how Vagifem works. Vagifem may also affect how your other medicines work.

- If you are going to have surgery or will be on bed rest

You may need to stop using Vagifem.

- If you are breast feeding

The hormone in Vagifem can pass into your milk.

How should I use Vagifem?

Vagifem is a tablet that you place in your vagina with an applicator.

- Take the dose recommended by your healthcare provider and talk to him or her about how well that dose is working for you
- Estrogens should be used at the lowest dose possible for your treatment only as long as needed

You and your healthcare provider should talk regularly (for example, every 3 to 6 months) about the dose you are taking and whether you still need treatment with Vagifem.

Step 1: Tear off a single applicator.

Step 2: Separate the plastic wrap and remove the applicator from the plastic wrap as shown in Figure A.

Figure A

Step 3: Hold the applicator so that the finger of one hand can press the applicator plunger as shown in Figure B.

Figure B

Step 4: Next select the best position for vaginal insertion of Vagifem (estradiol vaginal tablets) that is most comfortable for you. See suggested reclining Figure C or standing Figure D position illustrated below:

Figure C
Figure D

Step 5: Using the other hand, guide the applicator gently and comfortably through the vaginal opening (see Figures C and D above). If the tablet has come out of the applicator prior to insertion, carefully put it back into the applicator for insertion. Please keep your hands clean while handling the tablet.

Step 6: The applicator should be inserted (without forcing) as far as comfortably possible, or until half of the applicator is inside your vagina, whichever is less.

Step 7: Once the tablet-filled applicator has been inserted, gently press the plunger until the plunger is fully depressed. This will eject the tablet inside your vagina where it will dissolve slowly over several hours.

Step 8: After depressing the plunger, gently remove the applicator and dispose of it the same way you would a plastic tampon applicator. The applicator is of no further use and should be discarded properly. Insertion may be done at any time of the day. It is advisable to use the same time daily for all applications of Vagifem (estradiol vaginal tablets). If you have any questions, please consult your healthcare provider or pharmacist.

Dosage

Vagifem therapy consists of the following dosing regimen:

One (1) Vagifem tablet inserted vaginally once daily for the first two (2) weeks, then one (1) tablet inserted twice weekly (for example Tuesday and Friday) for as long as you use Vagifem.

What are the possible side effects of Vagifem?

Vagifem is only used in the vagina; however, the risks associated with oral estrogens should be taken into account.

Side effects are grouped by how serious they are and how often they happen when you are treated.

Serious but less common side effects include:

- Breast cancer
- Cancer of the uterus
- Stroke
- Heart attack
- Blood clots
- Dementia
- Gallbladder disease
- Ovarian cancer
- High blood pressure
- Liver problems
- High blood sugar
- Enlargement of benign tumors of the uterus (“fibroids”)

Some of the warning signs of serious side effects include:

- Breast lumps
- Unusual vaginal bleeding
- Dizziness and faintness
- Changes in speech
- Severe headaches
- Chest pain
- Shortness of breath
- Pains in your legs
- Changes in vision
- Vomiting
- Yellowing of the skin, eyes or nail beds

Call your healthcare provider right away if you get any of these warning signs, or any other unusual symptoms that concern you.

Less serious, but common, side effects include:

- Headache
- Breast pain
- Irregular vaginal bleeding or spotting
- Stomach/abdominal cramps, bloating
- Nausea and vomiting
- Hair loss
- Fluid retention
- Vaginal yeast infection

These are not all the possible side effects of Vagifem. For more information, ask your healthcare provider or pharmacist for advice about side effects. You may report side effects to FDA at 1-800-FDA-1088.

What can I do to lower my chances of a serious side effect with Vagifem?

- Talk with your healthcare provider regularly about whether you should continue using Vagifem
- If you have a uterus, talk with your healthcare provider about whether the addition of a progestin is right for you

The addition of a progestin is generally recommended for a woman with a uterus to reduce the chance of getting cancer of the uterus. See your healthcare provider right away if you get vaginal bleeding while using Vagifem.

- Have a pelvic exam, breast exam and mammogram (breast X-ray) every year unless your healthcare provider tells you something else

If members of your family have had breast cancer or if you have ever had breast lumps or an abnormal mammogram, you may need to have breast exams more often.

- If you have high blood pressure, high cholesterol (fat in the blood), diabetes, are overweight, or if you use tobacco, you may have higher chances for getting heart disease

Ask your healthcare provider for ways to lower your chances for getting heart disease.

General information about the safe and effective use of Vagifem.

Medicines are sometimes prescribed for conditions that are not mentioned in patient information leaflets. Do not use Vagifem for conditions for which it was not prescribed. Do not give Vagifem to other people, even if they have the same symptoms you have. It may harm them. Keep Vagifem out of the reach of children.

This leaflet provides a summary of the most important information about Vagifem. If you would like more information, talk with your healthcare provider or pharmacist. You can ask for information about Vagifem that is written for health professionals. You can get more information by calling the toll free number 1-888-824-4336.

What are the ingredients in Vagifem?

Vagifem (estradiol vaginal tablets) are small, white, film-coated tablets containing estradiol. Each tablet also contains hypromellose, lactose monohydrate, maize starch and magnesium stearate. The film coating contains hypromellose and polyethylene glycol.

Each Vagifem tablet is contained in a disposable applicator, packaged in a blister pack. Cartons contain 8 or 18 applicators with inset tablets.

Store at 25ºC (77ºF); excursions permitted to 15ºC - 30ºC (59ºF - 86ºF). Do not refrigerate.

[see USP Controlled Room Temperature].

Vagifem® is a registered trademark owned by Novo Nordisk FemCare AG.

© 2003-2011 Novo Nordisk

Date of Issue: May 18, 2011

Version: 7

For Information contact:

Novo Nordisk Inc.

100 College Road West

Princeton, NJ 08540, USA

1-888-824-4336

Manufactured by:

Novo Nordisk A/S

2880 Bagsvaerd, Denmark

Additional barcode labeling by:
Physicians Total Care, Inc.
Tulsa, Oklahoma 74146

Principal Display panel - VAGIFEM 10 MCG

NDC 54868-6182-0

Vagifem® 10mcg

(estradiol vaginal tablets)

8 vaginal tablets